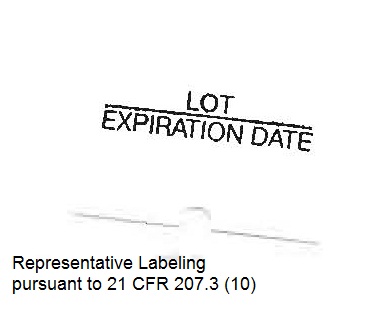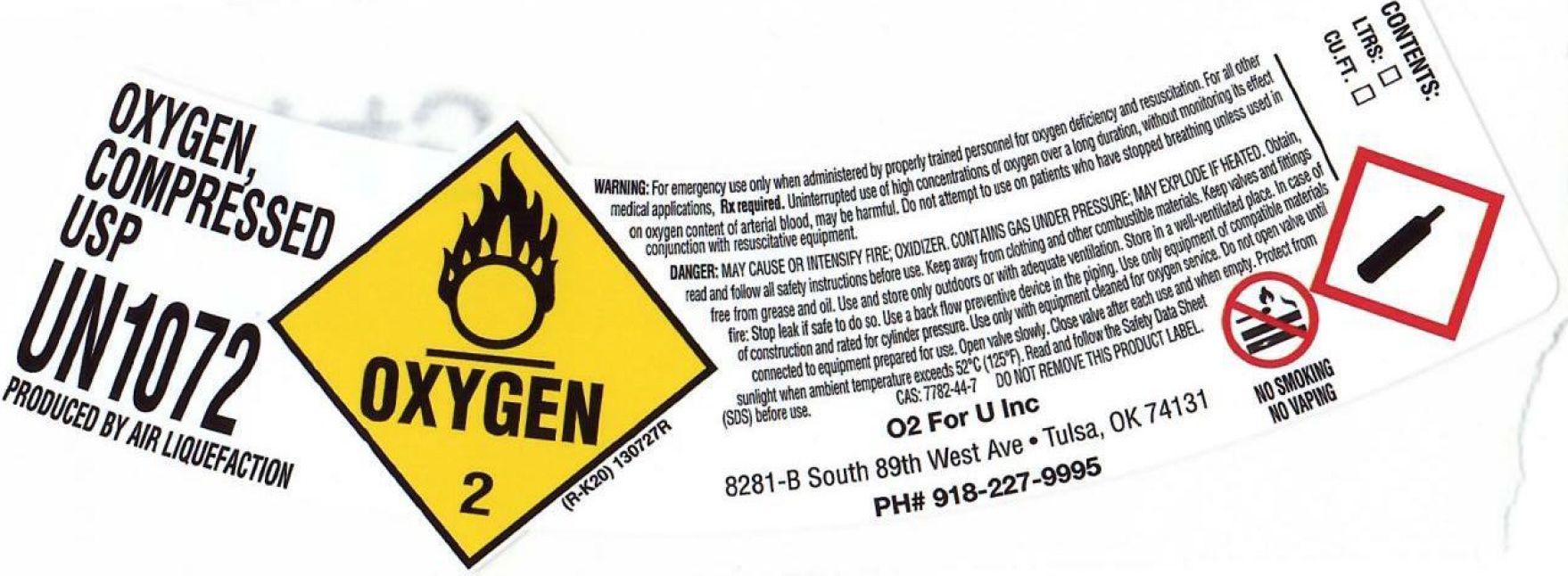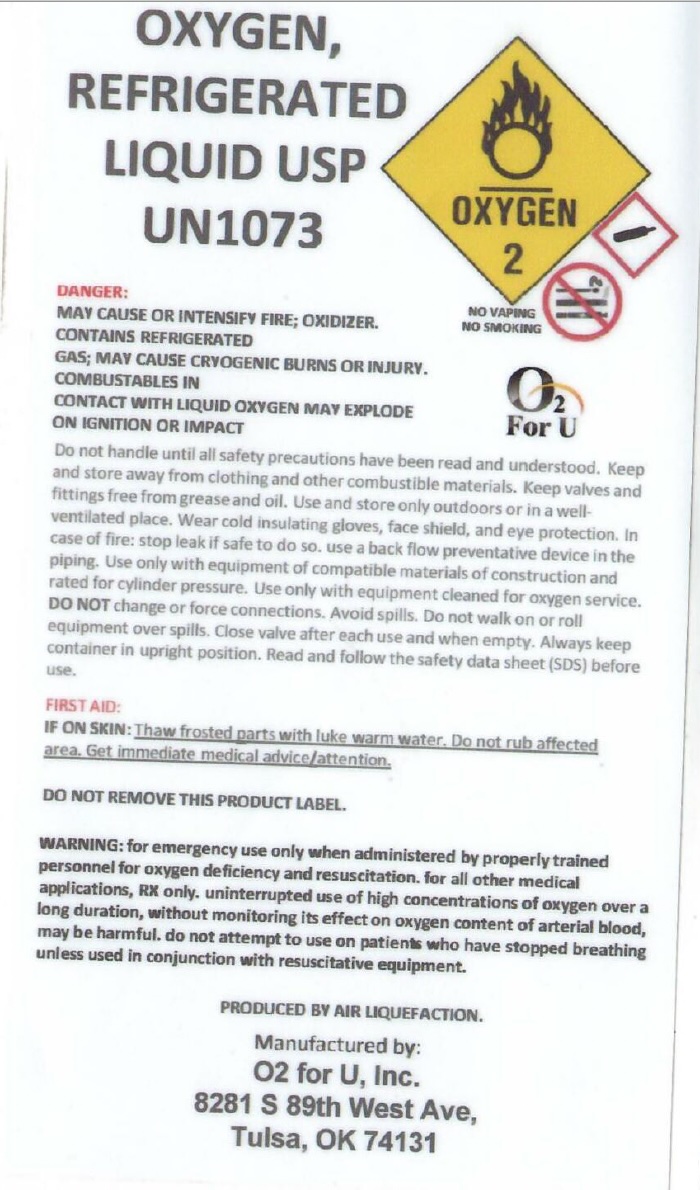 DRUG LABEL: Oxygen
NDC: 20175-072 | Form: GAS
Manufacturer: O2 for U, Inc.
Category: prescription | Type: HUMAN PRESCRIPTION DRUG LABEL
Date: 20251231

ACTIVE INGREDIENTS: OXYGEN 99 L/100 L

Oxygen, USP

Principal for Oxygen Product

OXYGEN, COMPRESSED

USP

UN1072

PRODUCED BY AIR LIQUEFACTION

⚠️ WARNING: For emergency use only when administered by properly trained personnel for oxygen deficiency and resuscitation. For all other medical applications, Rx required. Uninterrupted use of high concentrations of oxygen over a long duration, without monitoring its effect on oxygen content of arterial blood, may be harmful. Do not attempt to use on patients who have stopped breathing unless used in conjunction with resuscitative equipment.

DANGER: MAY CAUSE OR INTENSIFY FIRE; OXIDIZER. CONTAINS GAS UNDER PRESSURE; MAY EXPLODE IF HEATED. Obtain special instructions before use. Keep away from clothing and other combustible materials. Keep valves and fittings free from grease and oil. Use and store only outdoors or in a well-ventilated place. In case of fire: Stop leak if safe to do so. Use a back flow preventive device in the piping. Use only equipment of compatible materials of construction and rated for cylinder pressure. Use only equipment cleaned for oxygen service. Do not open valve until connected to equipment prepared for use. Open valve slowly. Close valve after each use and when empty. Protect from sunlight when ambient temperature exceeds 52°C (125°F). Read and follow the Safety Data Sheet (SDS) before use.

CAS: 7782-44-7

DO NOT REMOVE THIS PRODUCT LABEL

NO SMOKING

NO VAPING

O2 For U Inc

8281-B South 89th West Ave • Tulsa, OK 74131

PH# 918-227-9995

CONTENTS:

Liters ☐ CU FT ☐

OXYGEN,

REFRIGERATED

LIQUID USP

UN1073

DANGER:

MAY CAUSE OR INTENSIFY FIRE; OXIDIZER.

CONTAINS REFRIGERATED GAS; MAY CAUSE CRYOGENIC BURNS OR INJURY.

COMBUSTIBLES IN CONTACT WITH LIQUID OXYGEN MAY EXPLODE ON IGNITION OR IMPACT.

Do not handle until all safety precautions have been read and understood. Keep and store away from clothing and other combustible materials. Keep valves and fittings free from grease and oil. Use and store only outdoors or in a well-ventilated place. Wear cold insulating gloves, face shield, and eye protection. In case of fire: Stop leak if safe to do so. Use a back flow preventative device in the piping. Use only with equipment of compatible materials of construction and rated for cylinder pressure. Use only with equipment cleaned for oxygen service. DO NOT change or force connections. Avoid spills. Do not walk on or roll equipment over spills. Close valve after each use and when empty. Always keep container in upright position. Read and follow the safety data sheet (SDS) before use.

FIRST AID:

IF ON SKIN: Thaw frosted parts with luke warm water. Do not rub affected area. Get immediate medical advice/attention.

DO NOT REMOVE THIS PRODUCT LABEL.

WARNING: for emergency use only when administered by properly trained personnel for oxygen deficiency and resuscitation. for all other medical applications, Rx only. Uninterrupted use of high concentrations of oxygen over a long duration, without monitoring its effect on oxygen content of arterial blood, may be harmful. do not attempt to use on patients who have stopped breathing unless used in conjunction with resuscitative equipment.

PRODUCED BY AIR LIQUEFACTION.

Manufactured by:

O2 for U, Inc.

8281 S 89th West Ave.

Tulsa, OK 74131

NO VAPING

NO SMOKING